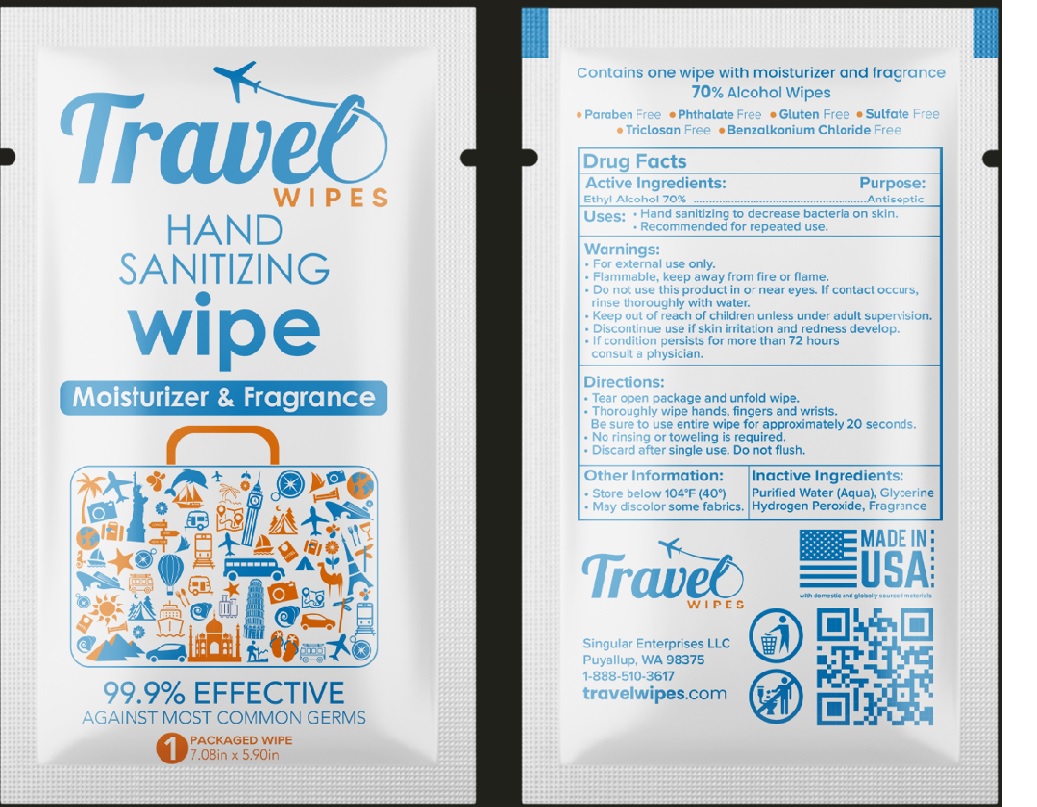 DRUG LABEL: Travel Wipes Moisturizer and fragrance
NDC: 81428-074 | Form: CLOTH
Manufacturer: SINGULAR ENTERPRISES LLC
Category: otc | Type: HUMAN OTC DRUG LABEL
Date: 20250606

ACTIVE INGREDIENTS: ALCOHOL 70 mL/100 mL
INACTIVE INGREDIENTS: WATER; GLYCERIN; HYDROGEN PEROXIDE; LEMON TERPENES

Active Ingredient (s)

Ethyl alcohol 70%

Purpose

Antiseptic

Uses

Hand sanitizing to decrease bacteria on skin. Recommended for repeated use.

Warnings

- For external use only.
- Flammable, keep away from fire or flame.
- Do not use this product in or near eyes. If contact occurs, rinse thoroughly with water.
- Keep out of reach of children unless under adult supervision.
- Discontinue use if skin irritation and redness develop.
- If condition persists for more than 72 hours consult a physician.

Directions

- Tear open package and unfold wipe.
- Thoroughly wipe hands fingers and wrists.
- Be sure to use entire wipe for approximately 20 seconds.
- No rinsing or toweling is required.
- Discard after single use. Do not flush.

Inactive Ingredients.

Purified Water, glycerine, hydrogen peroxide, fragrance

Other information (if applicable)

- Store below 104°F (40°)
- May discolor some fabrics.